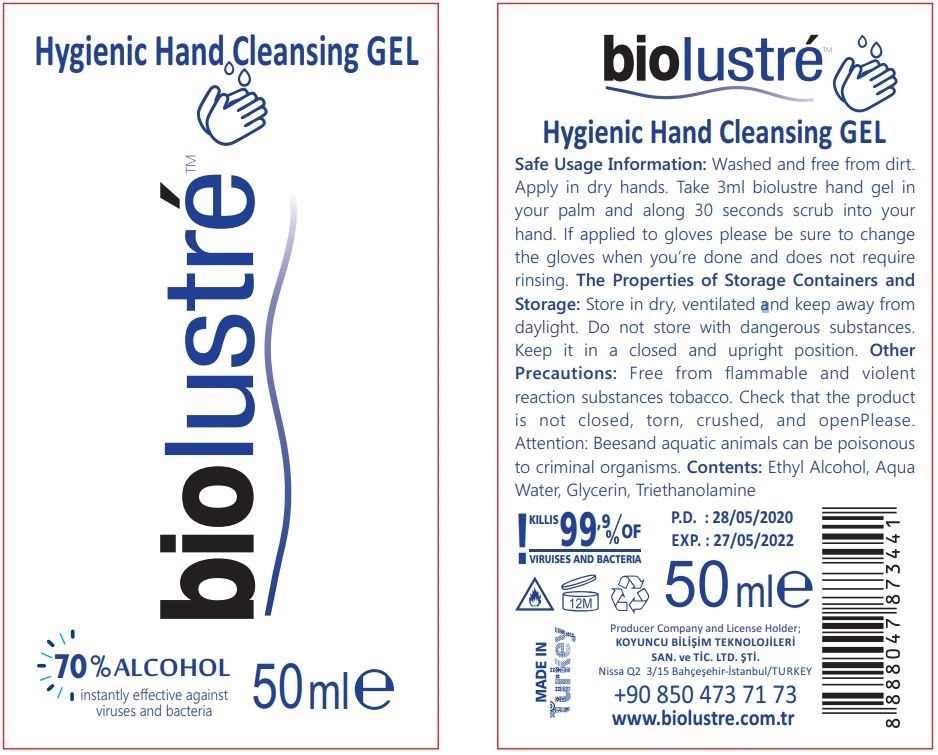 DRUG LABEL: Biolustre Hygienic Hand Cleansing Gel
NDC: 80371-104 | Form: GEL
Manufacturer: KOYUNCU BILISIM TEKNOLOJILERI SANAYI VE TICARET LIMITED SIRKETI
Category: otc | Type: HUMAN OTC DRUG LABEL
Date: 20200928

ACTIVE INGREDIENTS: ALCOHOL 70 mL/100 mL
INACTIVE INGREDIENTS: GLYCERIN; TROLAMINE; WATER; CARBOMER 940

ACTIVE INGREDIENT

Alcohol 70% v/w

PURPOSE

Antiseptic

INDICATIONS AND USAGE

Used for antibacterial hand skin, prevent bacteria.

WARNINGS

For external use only. Flammable. Keep away from fire.

DO NOT USE

• Keep away from fire.
• Do not wipe your eyes.
• Do not throw into the toilet (not soluble in water).

WHEN USING

• Please wait until the alcohol has completely evaporated after wiping.
• Before use, check whether the packaging is intact. Do not use if it is damaged.

Stop use and ask a doctor for those with alcohol allergy or sensitive skin.

Keep out of reach of children.

STORAGE AND HANDLING

• Store between 15-30°C (59-86°F).
• Avoid freezing and excessive heat above 40°C (104°F).

INACTIVE INGREDIENT

Water, Glycerin, Carbomer, Triethanolamine

DOSAGE AND ADMINISTRATION

Use it as needed, after following the usage instructions. For external use only.